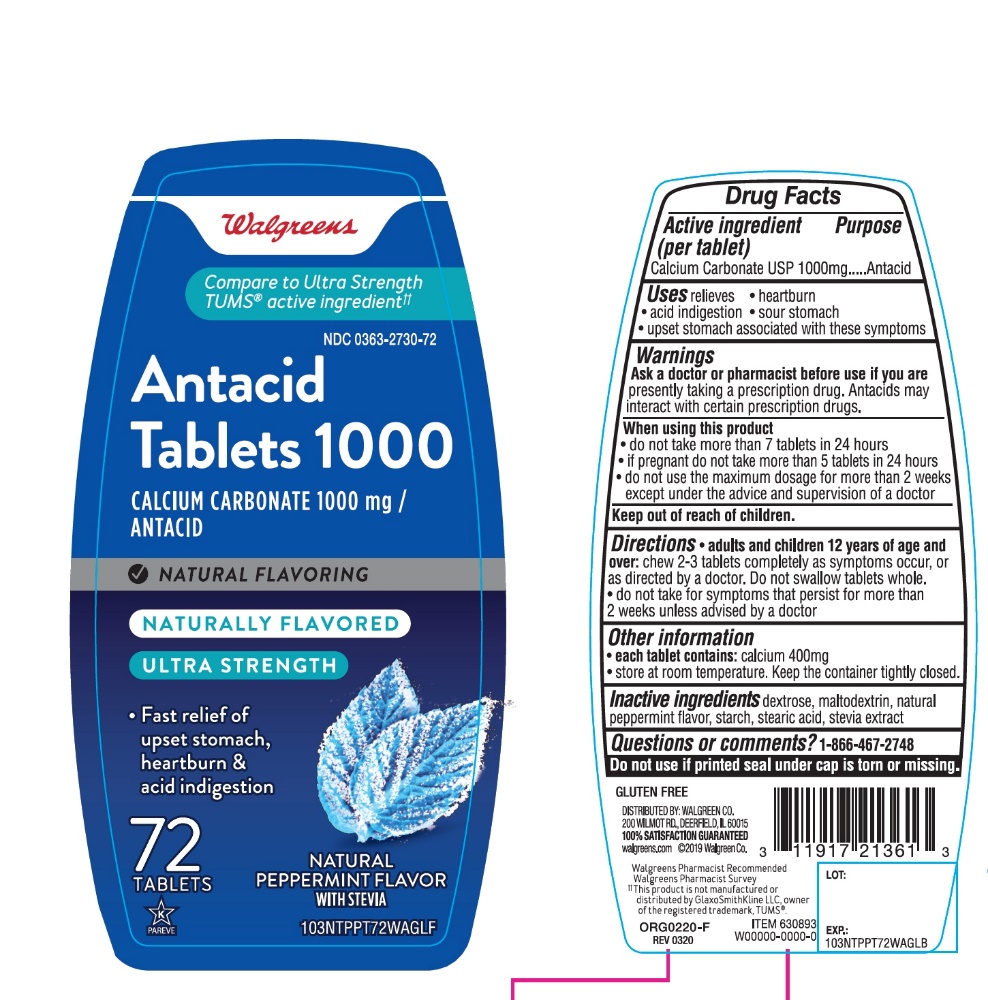 DRUG LABEL: ULTRA STRENGTH Antacid
NDC: 0363-2730 | Form: TABLET, CHEWABLE
Manufacturer: WALGREEN CO
Category: otc | Type: HUMAN OTC DRUG LABEL
Date: 20251125

ACTIVE INGREDIENTS: CALCIUM CARBONATE 1000 mg/1 1
INACTIVE INGREDIENTS: DEXTROSE, UNSPECIFIED FORM; MALTODEXTRIN; PEPPERMINT; STARCH, CORN; STEARIC ACID; STEVIA REBAUDIANA LEAF

Ultra Strength 72 Chewable Tablets Drug Facts

Active ingredient (per tablet)

Calcium Carbonate USP 1000mg

Purpose

Antacid

Uses

relieves

- heartburn
- acid indigestion
- sour stomach
- upset stomach associated with these symptoms

Ask a doctor or pharmacist before use if you are

presently taking a prescription drug. Antacids may interact with certain prescription drugs.

When using this product

- do not take more than 7 tablets in 24 hours
- If pregnant do not take more than 5 tablets in 24 hours
- do not use the maximum dosage for more than 2 weeks except under the advice and supervision of a doctor

Directions

- adults and children 12 years of age and over:chew 2-3 tablets completely as symptoms occur, or as directed by a doctor. Do not swallow tablets whole.
- do not take for symptoms that persist for more than 2 weeks unless advised by a doctor.

Other information

- each tablets contains:calcium 400mg
- Store at room temperature. Keep the container tightly closed.

Inactive ingredients

dextrose, maltodextrin, natural peppermint flavor, starch, stearic acid, stevia extract.

Questions or comments?

1-866-467-2748

Safety Sealed

Do not use if printed seal under cap is torn or missing.

Package/Label Principal Display Panel

Compare to the Ultra Strength TUMS®active ingredient††

NDC0363-2730-72

Antacid Tablets 1000

CALCIUM CARBONATE 1000 mg /

ANTACID

- NATURAL FLAVORING

NATURALLY FLAVORED

ULTRA STRENGTH

Fast Relief of upset stomach ,

heartburn & acid indigestion

NATURAL PEPPERMINT FLAVOR

WITH STEVIA

72 Chewable Tablets

K PAREVE

GLUTEN FREE

DISTRIBUTED BY: WALGREENS CO.

200 Wilmot Rd., Deerfield, IL 60015

100% SATISFACTION GUARANTEED

walgreens.com ©2019 Walgreen Co.

Walgreens Pharmacist Recommended Walgreens Pharmacist Survey

††This product is not manufactured or distributed by GlaxoSmithKline LLC, owner of the registered trademark, TUMS®.

ORG0220-F

REV 0320

ITEM 630893

W00000-0000-0